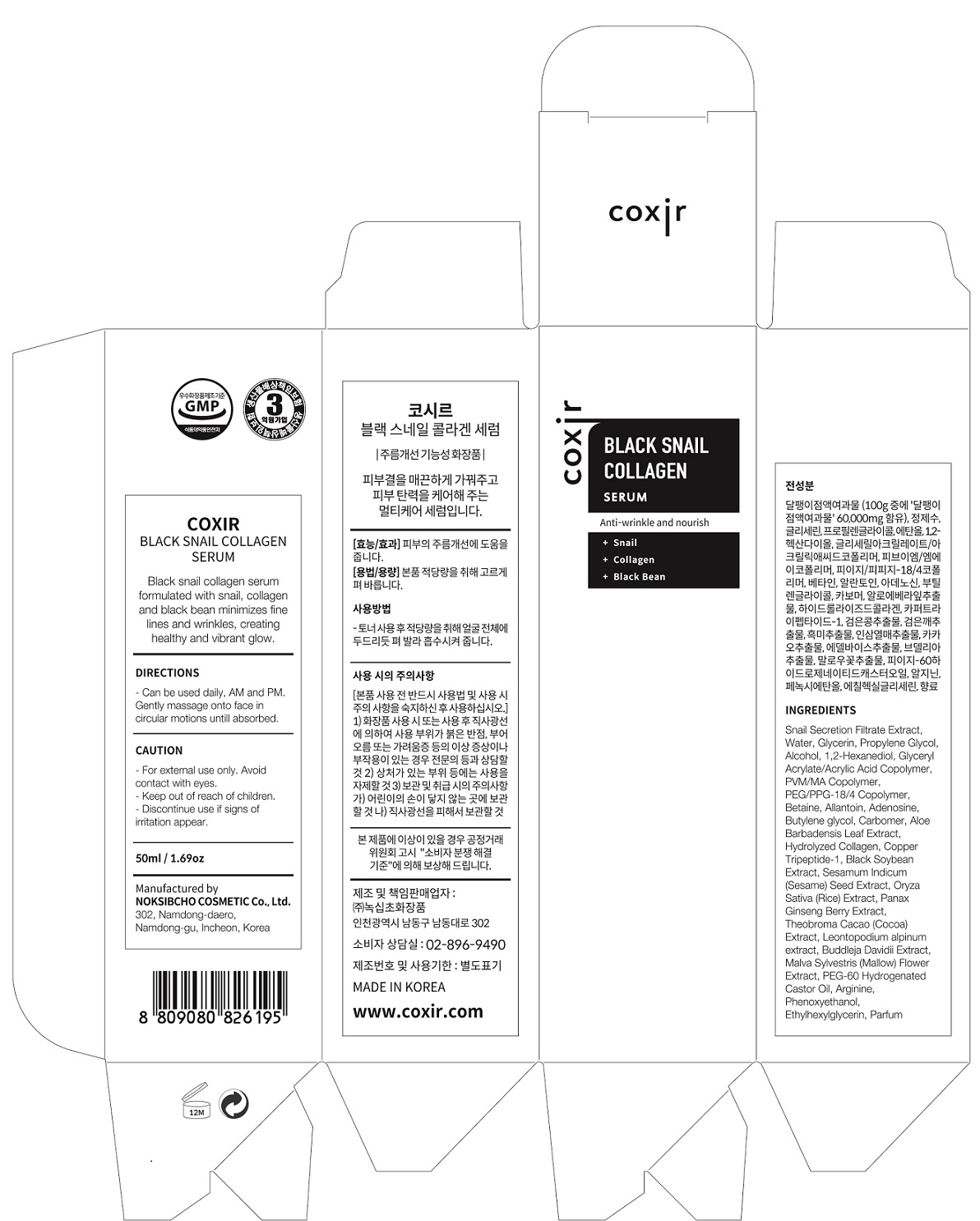 DRUG LABEL: Black Snail Collagen Serum
NDC: 73590-0013 | Form: LIQUID
Manufacturer: NOKSIBCHO cosmetic Co., Ltd.
Category: otc | Type: HUMAN OTC DRUG LABEL
Date: 20200314

ACTIVE INGREDIENTS: SNAIL, UNSPECIFIED 60 g/100 mL
INACTIVE INGREDIENTS: WATER; BUTYLENE GLYCOL

Drug Facts

ACTIVE INGREDIENT

Snail Secretion Filtrate

INACTIVE INGREDIENT

Water
Glycerin
Propylene Glycol
Alcohol
1,2-Hexanediol
Glycerin
Glyceryl Acrylate/Acrylic Acid Copolymer
Propylene Glycol
PVM/MA Copolymer
PEG/PPG-18/4 Copolymer
Betaine
Allantoin
Adenosine
Butylene glycol
Carbomer
Aloe Barbadensis Leaf Extract
Hydrolyzed Collagen
Copper Tripeptide-1
Black Soybean Extract
Sesamum Indicum (Sesame)
Seed Extract
Oryza Sativa (Rice) Extract
Panax Ginseng Berry Extract
Leontopodium alpinum extract
Buddleja Davidii Extract
Malva Sylvestris (Mallow) Flower Extract
Theobroma Cacao (Cocoa) Extract
PEG-60 Hydrogenated Castor Oil
Arginine
Phenoxyethanol
Ethylhexylglycerin
Parfum

PURPOSE

anti-wrinkle and nourish

keep out of reach of the children

INDICATIONS AND USAGE

apply proper amount and gently massage

WARNINGS

For external use only
When using this product

■ if the following symptoms occurs after use, stop use and consult with a skin specialist

red specks, swelling, itching

■ don’t use on the part where there is injury, eczema, or dermatitis

Keep out of reach of children

■ if swallowed, get medical help or contact a person control center immediately

DOSAGE AND ADMINISTRATION

for external use only